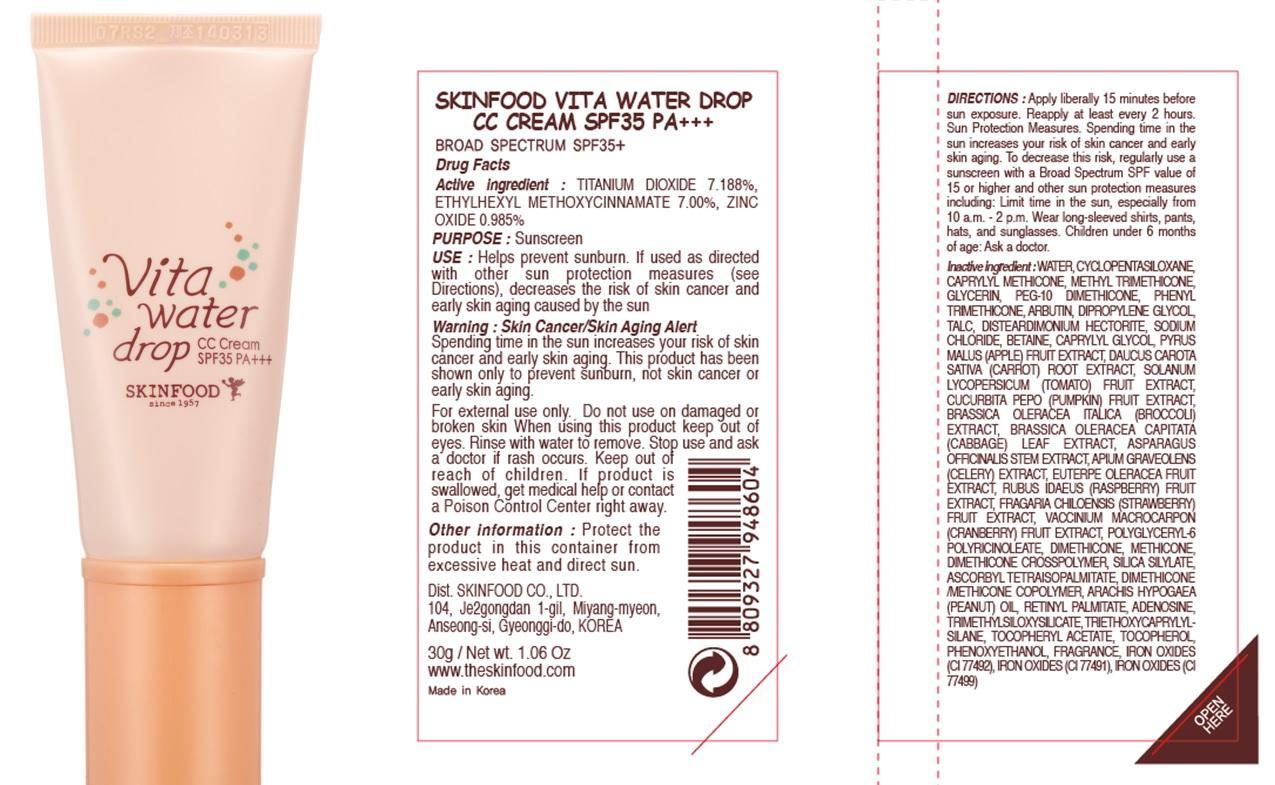 DRUG LABEL: VITA WATER DROP CC
NDC: 76214-048 | Form: CREAM
Manufacturer: SKINFOOD CO., LTD.
Category: otc | Type: HUMAN OTC DRUG LABEL
Date: 20141103

ACTIVE INGREDIENTS: TITANIUM DIOXIDE 2.15 g/30 g; OCTINOXATE 2.1 g/30 g; ZINC OXIDE 0.29 g/30 g
INACTIVE INGREDIENTS: WATER; GLYCERIN

ACTIVE INGREDIENT

Active ingredient: TITANIUM DIOXIDE 7.188%, ETHYLHEXYL METHOXYCINNAMATE 7.00%, ZINC OXIDE 0.985%

INACTIVE INGREDIENT

WATER, CYCLOPENTASILOXANE, CAPRYLYL METHICONE, METHYL TRIMETHICONE, GLYCERIN, PEG-10 DIMETHICONE, PHENYL TRIMETHICONE, ARBUTIN, DIPROPYLENE GLYCOL, TALC, DISTEARDIMONIUM HECTORITE, SODIUM CHLORIDE, BETAINE, CAPRYLYL GLYCOL, PYRUS MALUS (APPLE) FRUIT EXTRACT, DAUCUS CAROTA SATIVA (CARROT) ROOT EXTRACT, SOLANUM LYCOPERSICUM (TOMATO) FRUIT EXTRACT, CUCURBITA PEPO (PUMPKIN) FRUIT EXTRACT, BRASSICA OLERACEA ITALICA (BROCCOLI) EXTRACT, BRASSICA OLERACEA CAPITATA (CABBAGE) LEAF EXTRACT, ASPARAGUS OFFICINALIS STEM EXTRACT, APIUM GRAVEOLENS (CELERY) EXTRACT, EUTERPE OLERACEA FRUIT EXTRACT, RUBUS IDAEUS (RASPBERRY) FRUIT EXTRACT, FRAGARIA CHILOENSIS (STRAWBERRY) FRUIT EXTRACT, VACCINIUM MACROCARPON (CRANBERRY) FRUIT EXTRACT, POLYGLYCERYL-6 POLYRICINOLEATE, DIMETHICONE, METHICONE, DIMETHICONE CROSSPOLYMER, SILICA SILYLATE, ASCORBYL TETRAISOPALMITATE, DIMETHICONE/METHICONE COPOLYMER, ARACHIS HYPOGAEA (PEANUT) OIL, RETINYL PALMITATE, ADENOSINE, TRIMETHYLSILOXYSILICATE, TRIETHOXYCAPRYLYLSILANE, TOCOPHERYL ACETATE, TOCOPHEROL, PHENOXYETHANOL, FRAGRANCE, IRON OXIDES (CI 77492), IRON OXIDES (CI 77491), IRON OXIDES (CI 77499)

PURPOSE

PURPOSE: Sunscreen

WARNINGS

Warning:
Skin Cancer/Skin Aging Alert
Spending time in the sun increases your risk of skin cancer and early skin aging.
This product has been shown only to prevent sunburn, not skin cancer or early skin aging.

KEEP OUT OF REACH OF CHILDREN

USE

Helps prevent sunburn.
If used as directed with other sun protection measures (see Directions), decreases the risk of skin cancer and early skin aging caused by the sun

DIRECTIONS

Apply liberally 15 minutes before sun exposure.
Reapply at least every 2 hours. Sun Protection Measures.
Spending time in the sun increases your risk of skin cancer and early skin aging.
To decrease this risk, regularly use a sunscreen with a Broad Spectrum SPF value of 15 or higher and other sun protection measures including: Limit time in the sun, especially from 10 a.m. - 2 p.m.
Wear long-sleeved shirts, pants, hats, and sunglasses.
Children under 6 months of age: Ask a doctor.

Other information

Protect the product in this container from excessive heat and direct sun.